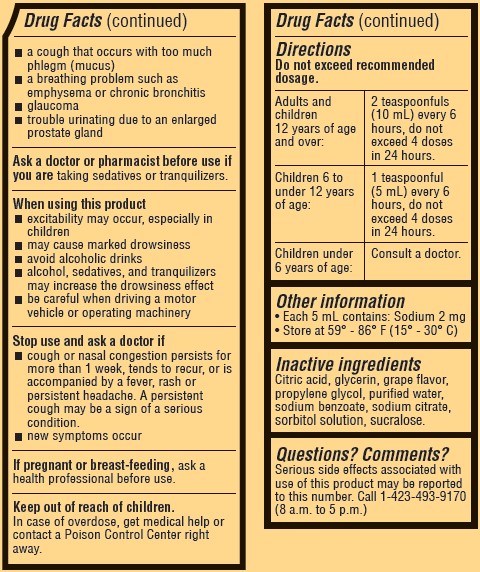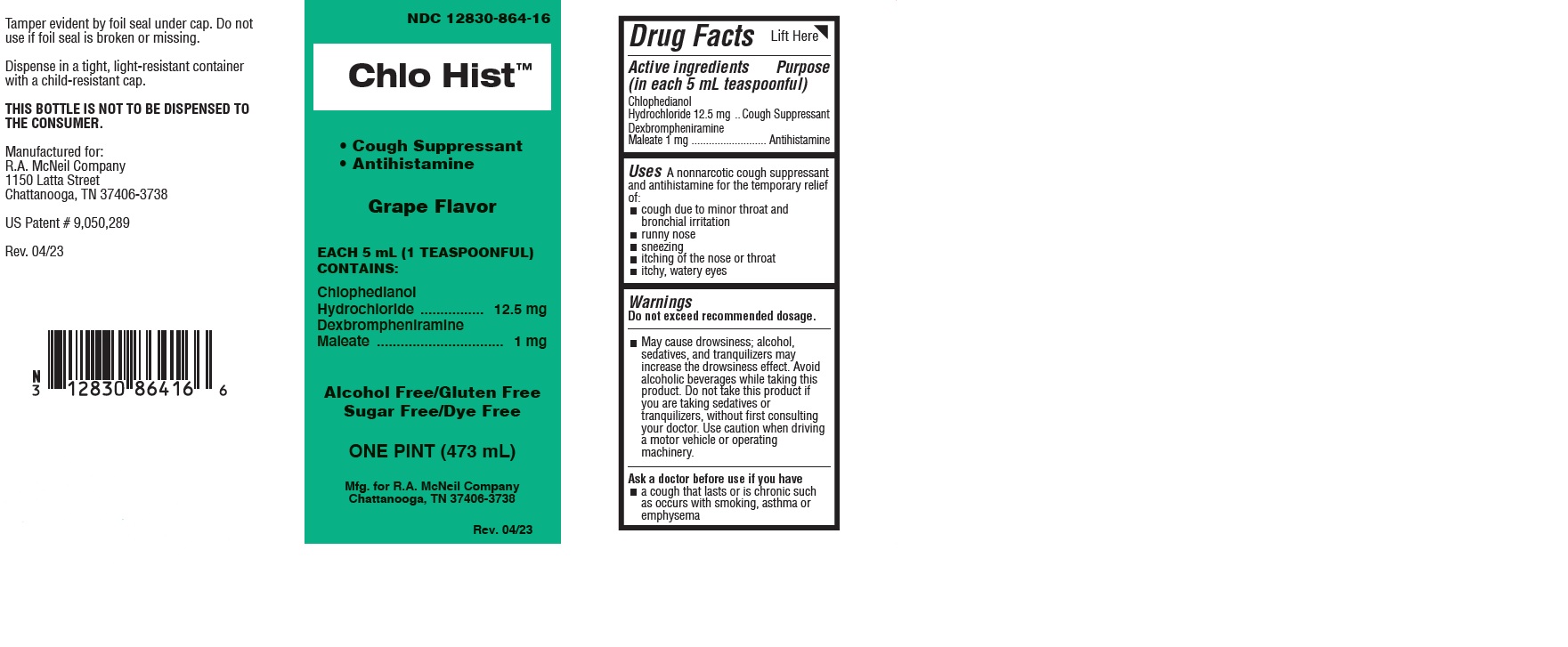 DRUG LABEL: Chlo Hist
NDC: 12830-864 | Form: LIQUID
Manufacturer: R. A. McNeil Company
Category: otc | Type: HUMAN OTC DRUG LABEL
Date: 20251015

ACTIVE INGREDIENTS: CHLOPHEDIANOL HYDROCHLORIDE 12.5 mg/5 mL; DEXBROMPHENIRAMINE MALEATE 1 mg/5 mL
INACTIVE INGREDIENTS: SODIUM BENZOATE; CITRIC ACID MONOHYDRATE; GLYCERIN; PROPYLENE GLYCOL; WATER; SODIUM CITRATE; SUCRALOSE; SORBITOL

Chlo Hist Oral Solution

Drug Facts

Active ingredients

(in each 5 mL teaspoonful)

Chlophedianol Hydrochloride 12.5 mg

Dexbrompheniramine Maleate 1 mg

Purpose

Cough Suppressant

Antihistamine

INDICATIONS AND USAGE

Uses A nonnaracotic cough suppressant and antihistamine for the temporary relief of:

- cough due to minor throat and bronchial irritation
- runny nose
- sneezing
- itching of the nose or throat
- itchy, watery eyes

Warnings

Do not exceed recommended dosage.

- May cause drowsiness; alcohol, sedatives, and tranquilizers may increase the drowsiness effect. Avoid alcoholic beverages while taking this product. Do not take this product if you are taking sedatives or tranquilizers, without first consulting your doctor. Use caution when diving a motor vehicle or operating machinery.

Ask a doctor before use if you have

- a cough that lasts or is chronic such as occurs with smoking, asthma or emphysema
- a cough that occurs with too much phlegm (mucus)
- a breathing problem such as emphysema or chronic bronchitis
- glaucoma
- trouble urinating due to an enlarged prostate gland

Ask a doctor or pharmacist before use if you are taking sedatives or tranquilizers.

When using this product

- excitability may occur, especially in children
- may cause marked drowsiness
- avoid alcoholic drinks
- alcohol, sedatives, and tranquilizes may increase the drowsiness effect
- be careful when driving a motor vehicle or operating machinery

Stop use and ask a doctor if

- cough or nasal congestion persists for more than 1 week, tends to recur, or is accompanied by a fever, rash or persistent headache. A persistent cough may be a sign of a serious condition.
- new symptoms occur

PREGNANCY OR BREAST FEEDING

If pregnant or breast-feeding, ask a health professional before use.

Keep out of reach of children.

In case of overdose, get medical help or contact a Poison Control Center right away.

Directions

Do not exceed recommended dosage.

Adults and children 12 years of age and over: | 2 teaspoonfuls (10 mL) every 6 hours, not to exceed 4 doses in 24 hours
Children 6 to under 12 years of age: | 1 teaspoonful (5 mL) every 6 hours, not to exceed 4 doses in 24 hours
Children under 6 years of age: | Consult a Physician.

Other information

Each 5 mL contains: Sodium 2 mg

Store at 59°-86°F (15°-30°C)

Inactive ingredients

itric Acid, Glycerin, Grape Flavor, Propylene Glycol, Purified Water, Sodium Benzoate, Sodium Citrate, Sorbitol Solution, Sucralose.

Questions? Comments?

Serious side effects associated with use of this product may be reported to this number. Call 1-423-493-9170 (8 a.m. to 5 p.m.)

Product Package Label for 473 mL

NDC 12830-864-16
Chlo HIst

Oral Solution

- Cough Suppressant
- Antihistamine

Grape Flavor

EACH 5 mL (1 TEASPOONFUL)

CONTAINS:

Chophedianol

Hydrochloride..................................12.5 mg

Dexbrompheniramine

Maleate................................................1 mg

Alcohol Free/Gluten Free

Sugar Free/Dye Free
ONE PINT (473 mL)

Mfg. for R.A. McNeil Company

Chattanooga, TN 37406-3738

Rev. 09/17

Tamper evident by foil seal under cap. Do not

use if foil seal is broken or missing.

Dispense in a tight, light-resistant container

with a child-resistant cap.

THIS BOTTLE IS NOT TO BE DISPENSED TO
THE CONSUMER.

Manufactured for:

R.A. McNeil Company

1150 Latta Street

Chattanooga, TN 37406-3738

US Patent # 9,050,289

Rev. 09/17